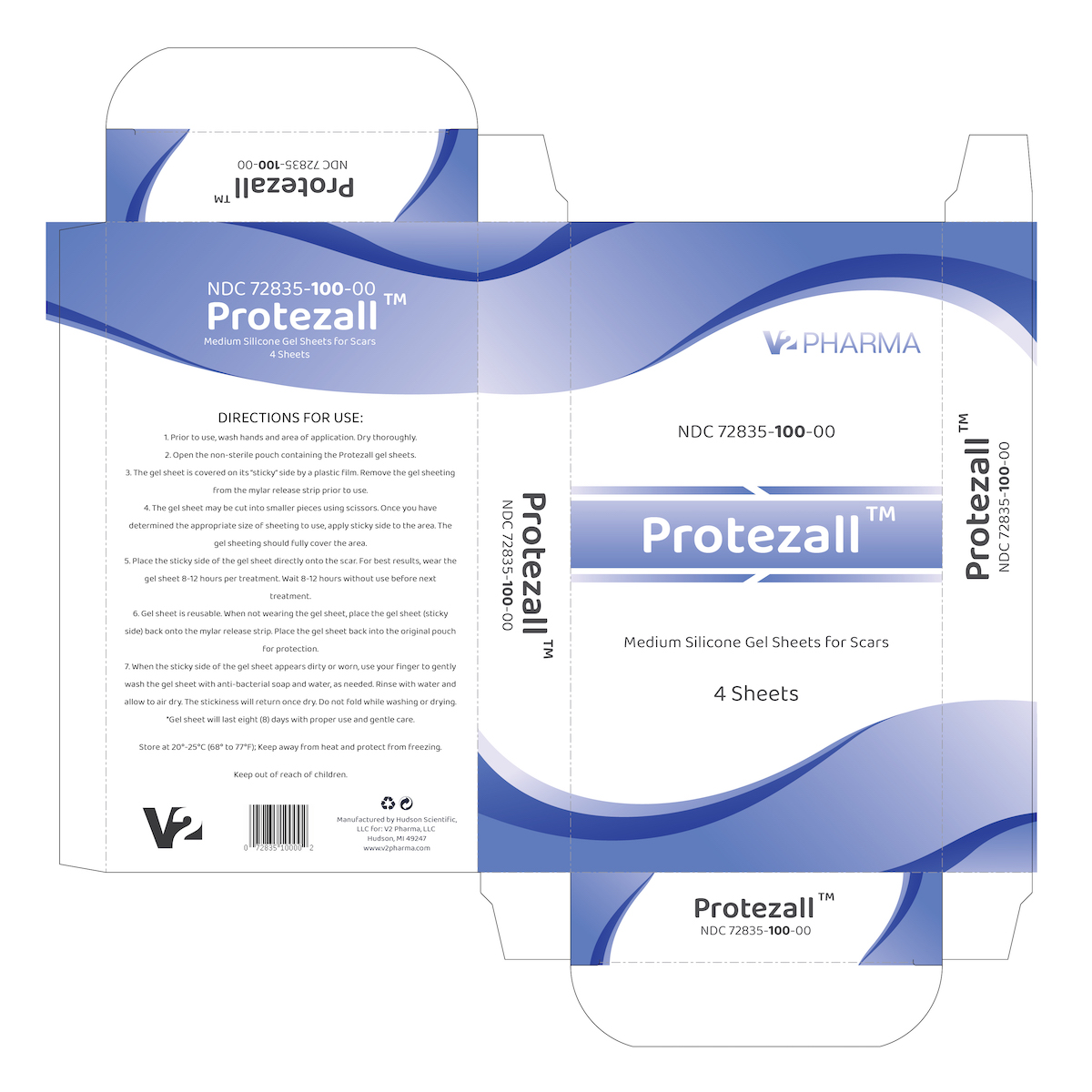 DRUG LABEL: Protezall
NDC: 72835-100
Manufacturer: V2 Pharma
Category: other | Type: MEDICAL DEVICE
Date: 20230627

Protezall medium silicone gel sheets for scars

Description

Protezall is a Silicone Gel Scar Dressing which fades and softens existing scars, as well as new hypertrophic keloids or scars. Protezall is very comfortable to wear, reusable and washable. Each of the enclosed sheets can last up to eight days with proper care.

Indications and Usage

For non-invasive management of both existing and new hypertrophic scars or keloids.

Contraindications:

Protezall is contraindicated for patients who are sensitive to silicone.

Warnings and Precautions:

For external use only.

Stop use in the event of itching, blisters, or skin irritation.

Do not apply to the surgical wound until at least 1 week after sutures, if any, have been removed. Do not use on open or unhealed wounds.

Clean skin surface before use. A rash may result if the skin surface has not been cleaned.

Each gel sheet can be reused for up to eight days. If adhesive side is dirty, wash it gently with a finger using antibacterial soap and water. Rince gently and allow the sheet to dry.

Protezall should not be shared with others.

Dosage & Administration:

Instructions for use:

1. Prior to use, wash hands and area of application. Dry thoroughly.
2. Open the non-sterile pouch containing the Protezall Gel Sheeting
3. The gel sheet is covered on its "sticky" side by a plastic film. Remove the gel sheeting from the mylar release strip prior to use.
4. The gel sheet may be cut into smaller pieces using scissors. Once you have determined the appropriate size of sheeting to use, apply sticky side to the area. The gel sheeting should fully cover the area.
5. Place the sticky side of the gel sheet directly onto the scar. For best results, wear the gel sheet 8-12 hours per treatment. Wait 8-12 hours without use before next treatment.
6. Gel sheet is reusable. When not wearing the gel sheet, place the gel sheet (sticky side) back onto the mylar release strip. Place the gel sheet back into the original pouch for protection.
7. When the sticky side of the gel sheet appears dirty or worn, use your finger to gently wash the gel sheet with anti-bacterial soap and water, as needed. Rince with water and allow to air dry. The stickiness will return once dry. Do not fold while washing or drying.

How Supplied:

Protezall is provided in a box containing four individually wrapped pouches, each containing one Gel Sheet.

Storage and Handling:

Store at 20-25C (68 to 77F). Keep away from heat and protect from freezing.

Adverse Reactions:

Although very rare, Protezall may cause skin irritations including redness, stinging or other irritations. Those effects should go away after use is discontinued.

Manufacturer:

Protezall is manufactured by Hudson Scientific LLC, Hudson Michigan for:

V2 Pharma LLC
103 W. Main St.
Hudson, MI 49247

Protezall Box

Protezall is sold in a box resembling the following: